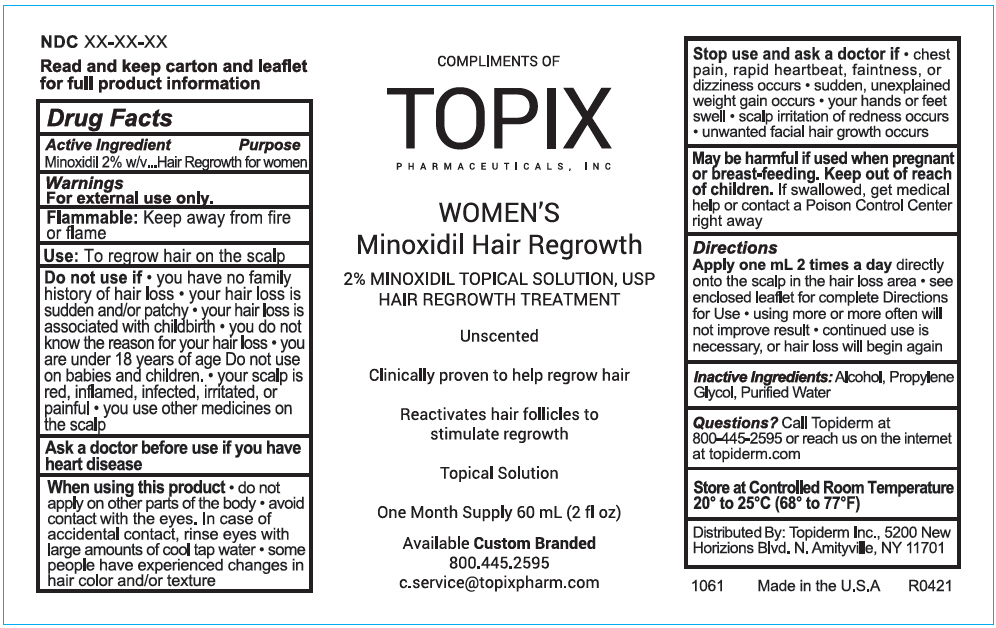 DRUG LABEL: Womens Minoxidil 
NDC: 51326-161 | Form: LIQUID
Manufacturer: Topiderm, Inc.
Category: otc | Type: HUMAN OTC DRUG LABEL
Date: 20210423

ACTIVE INGREDIENTS: MINOXIDIL 20 mg/1 mL
INACTIVE INGREDIENTS: ALCOHOL; PROPYLENE GLYCOL; WATER

Women's Minoxidil
Hair Growth System

Drug Facts

Active Ingredient

Minoxidil 2% w/v

Purpose

Hair Regrowth for women

Warnings

For external use only.

Flammable: Keep away from fire or flame

Use

To regrow hair on the scalp

WARNINGS

Do not use if

- you have no family history of hair loss
- your hair loss is sudden and/or patchy
- your hair loss is associated with childbirth
- you do not know the reason for your hair loss
- you are under 18 years of age Do not use on babies and children.
- your scalp is red, inflamed, infected, irritated, or painful
- you use other medicines on the scalp

Ask a doctor before use if you have heart disease

When using this product

- do not apply on other parts of the body
- avoid contact with the eyes. In case of accidental contact, rinse eyes with large amounts of cool tap water
- some people have experienced changes in hair color and/or texture

Stop use and ask a doctor if

- chest pain, rapid heartbeat, faintness, or dizziness occurs
- sudden, unexplained weight gain occurs
- your hands or feet swell
- scalp irritation of redness occurs
- unwanted facial hair growth occurs

PREGNANCY OR BREAST FEEDING

May be harmful if used when pregnant or breast-feeding.

Keep out of reach of children. If swallowed, get medical help or contact a Poison Control Center right away

Directions

Apply one mL 2 times a day directly onto the scalp in the hair loss area

- see enclosed leaflet for complete Directions for Use
- using more or more often will not improve result
- continued use is necessary, or hair loss will begin again

Inactive Ingredients

Alcohol, Propylene Glycol, Purified Water

Questions?

Call Topiderm at 800-445-2595 or reach us on the internet at topiderm.com

STORAGE AND HANDLING

Store at Controlled Room Temperature 20° to 25°C (68° to 77°F)

Distributed By: Topiderm Inc., 5200 New Horizions Blvd. N. Amityville, NY 11701

PRINCIPAL DISPLAY PANEL - 60 mL Bottle Label

COMPLIMENTS OF
TOPIX
PHARMACEUTICALS, INC

WOMEN'S
Minoxidil Hair Regrowth

2% MINOXIDIL TOPICAL SOLUTION, USP
HAIR REGROWTH TREATMENT

Unscented

Clinically proven to help regrow hair

Reactivates hair follicles to
stimulate regrowth

Topical Solution

One Month Supply 60 mL (2 fl oz)

Available Custom Branded
800.445.2595
c.service@topixpharm.com